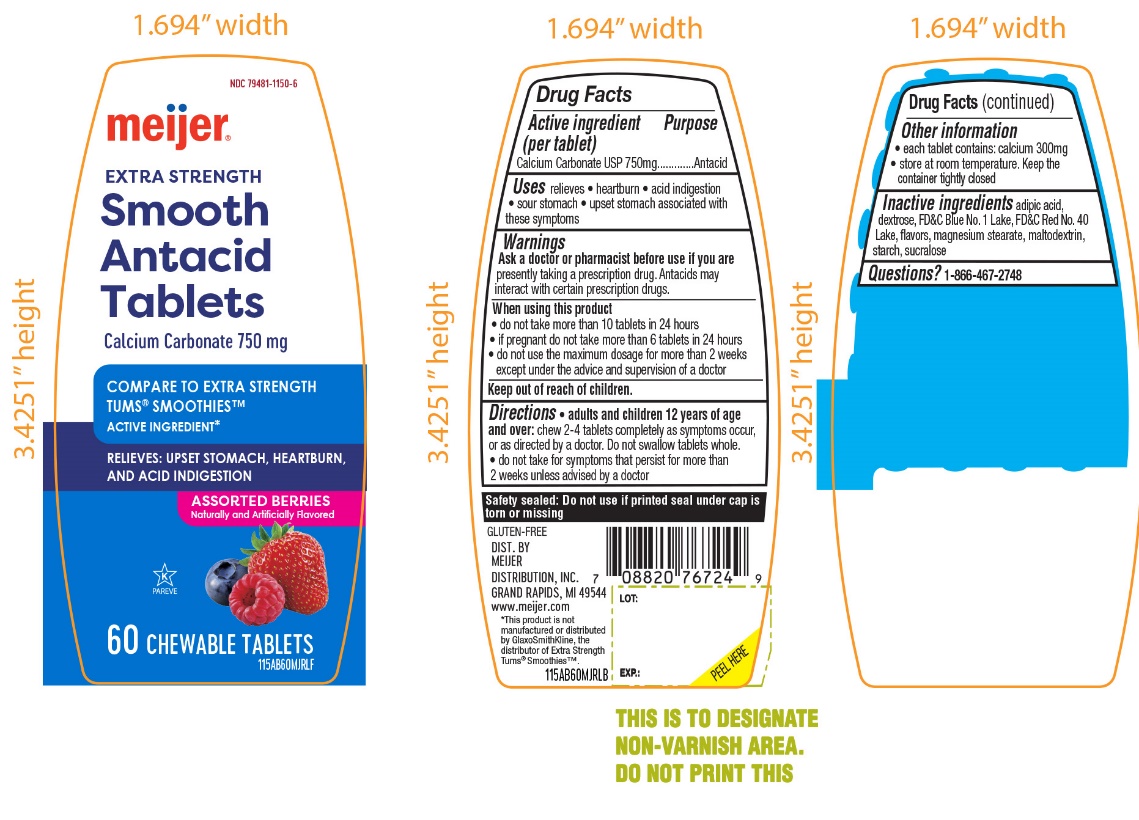 DRUG LABEL: Meijer Antacid Extra Strength

NDC: 79481-1150 | Form: TABLET, CHEWABLE
Manufacturer: MEIJER DISTRIBUTION INC.
Category: otc | Type: HUMAN OTC DRUG LABEL
Date: 20251024

ACTIVE INGREDIENTS: CALCIUM CARBONATE 750 mg/1 1
INACTIVE INGREDIENTS: ADIPIC ACID; DEXTROSE, UNSPECIFIED FORM; FD&C BLUE NO. 1; FD&C RED NO. 40; MAGNESIUM STEARATE; MALTODEXTRIN; STARCH, CORN; SUCRALOSE

Meijer Extra Strength Smooth Antacid 60 Chewable Tablets Drug Facts

Active ingredient (per tablet)

Calcium Carbonate USP 750mg

Purpose

Antacid

Uses

relieves

- heartburn
- acid indigestion
- sour stomach
- upset stomach associated with these symptoms

Ask a doctor or pharmacist before use if you are

presently taking a prescription drug. Antacids may interact with certain prescription drugs.

When using this product

- do not take more than 10 tablets in 24 hours
- if pregnant do not take more than 6 tablets in 24 hours
- do not use the maximum dosage for more than 2 weeks except under the advice and supervision of a doctor

Directions

- adults and children 12 years of age and over:chew 2-4 tablets as symptoms occur, or as directed by a doctor. Do not swallow tablets whole.
- do not take for symptoms that persist for more than 2 weeks unless advised by a doctor

Other information

- each tablet contains:calcium 300mg
- store at room temperature. Keep the container tightly closed.

Inactive ingredients

adipic acid, dextrose, FD&C Blue No. 1, FD&C Red No. 40, flavors, magnesium stearate, maltodextrin, starch, sucralose

Questions?

1-866-467-2748

Principal Display Panel

Meijer®

NDC#79481-1150-6

COMPARE TO EXTRA STRENGTH TUMS® SMOOTHIES™ ACTIVE INGREDIENT*

EXTRA STRENGTH

Smooth Antacid Tablets

Calcium Carbonate 750 mg

RELIEVES:

- UPSET STOMACH
- HEARTBURN
- ACID INDIGESTION

ASSORTED BERRY

Naturally and Artificially Flavored

GLUTEN FREE

60 CHEWABLE TABLETS

K PAREVE

DISTRIBUTED BY

MEIJER DISTRIBUTION, INC

GRAND RAPIDS, MI 49544

www.meijer.com

*This product is not manufactured or distributed by GlaxoSmithKline, the distributor of Extra Strength Tums®Smoothies™.